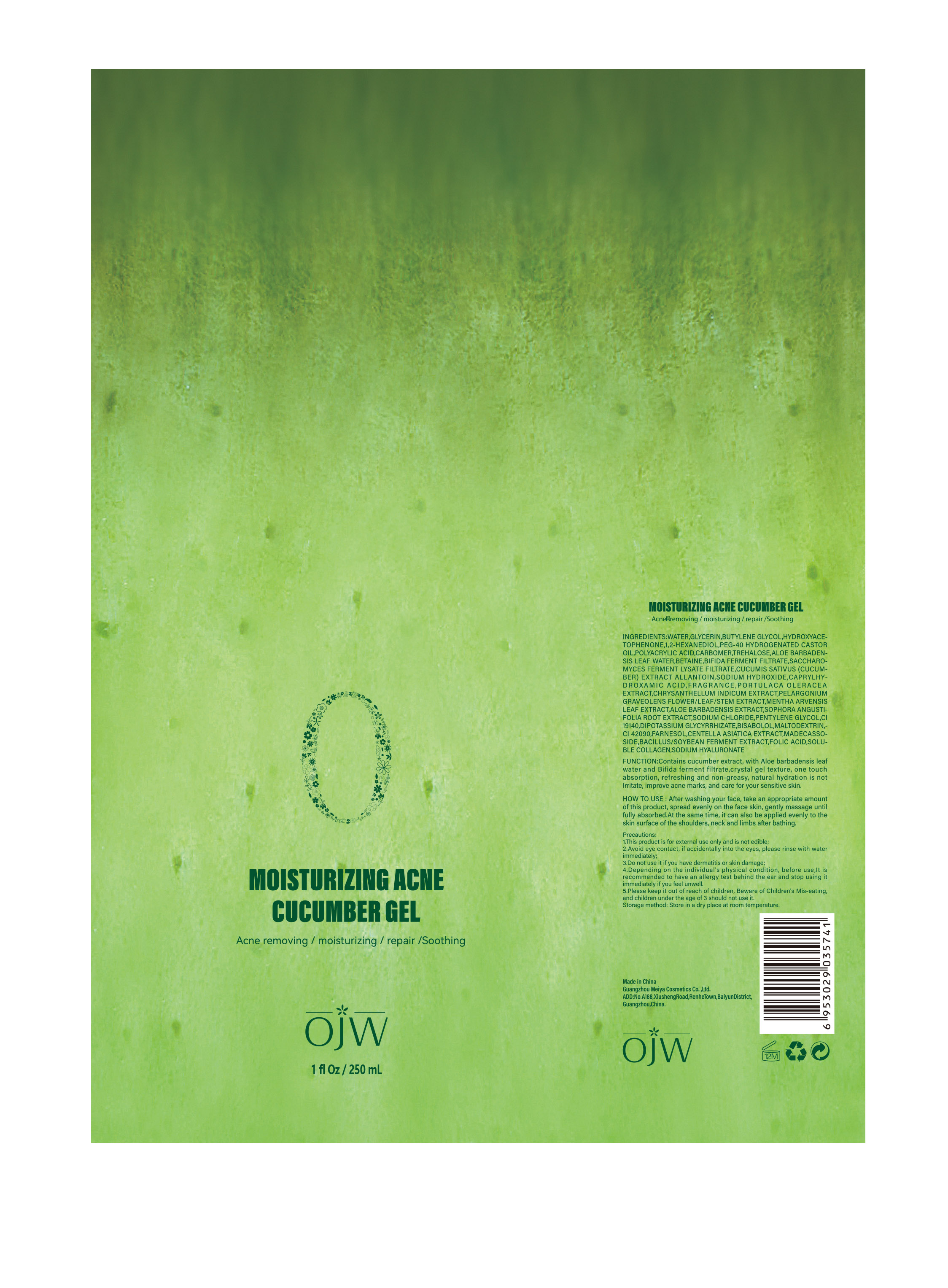 DRUG LABEL: Moisturizing acne
NDC: 84673-001 | Form: CHEWABLE GEL
Manufacturer: Guangzhou Meiya Cosmetics Co., Ltd.
Category: otc | Type: HUMAN OTC DRUG LABEL
Date: 20240901

ACTIVE INGREDIENTS: MADECASSOSIDE 0.3 g/1 mg
INACTIVE INGREDIENTS: TREHALOSE 0.12 g/1 mg; CAPRYLHYDROXAMIC ACID 0.05 g/1 mg; MALTODEXTRIN 0.08 g/1 mg; GLYCERIN 0.024 g/1 mg; FARNESOL 0.11 g/1 mg; SODIUM HYDROXIDE 0.135 g/1 mg; BETAINE 0.12 g/1 mg; FOLIC ACID 0.2 g/1 mg; ALLANTOIN 0.1 g/1 mg; SODIUM CHLORIDE 0.51 g/1 mg; HYDROXYACETOPHENONE 3 g/1 mg; BUTYLENE GLYCOL 0.04 g/1 mg; WATER 85 g/1 mg; POLYACRYLIC ACID (800000 MW) 0.2 g/1 mg; PENTYLENE GLYCOL 0.2 g/1 mg; 1,2-HEXANEDIOL 0.3 g/1 mg

ACTIVE INGREDIENT

ALOE BARBADENSIS LEAF WATER 3%

ALLANTOIN 2.9%

PORTULACA OLERACEA EXTRACT 1.8%

CHRYSANTHELLUM INDICUM EXTRACT 1.5%

SOPHORA ANGUSTIFOLIA ROOT EXTRACT 0.8%

CENTELLA ASIATICA EXTRACT 0.5%

MADECASSOSIDE 0.3%

PURPOSE

Function:Contains cucumber extract, with Aloe barbadensis leaf water and Bifida ferment filtrate,crystal gel texture, one touch absorption, refreshing and non-greasy, natural hydration is not Irritate, improve acne marks, and care for your sensitive skin.

INDICATIONS AND USAGE

HOW TO USE : After washing your face, take an appropriate amount of this product, spread evenly on the face skin, gently massage until fully absorbed.At the same time, it can also be applied evenly to the skin surface of the shoulders, neck and limbs after bathing.

WARNINGS

Precautions:

1. This product is for external use only and is not edible;

2. Avoid eye contact, if accidentally into the eyes, please rinse with water immediately;

3. Do not use it if you have dermatitis or skin damage;

4. Depending on the individual's physical condition, before use,It is recommended to have an allergy test behind the ear and stop using it immediately if you feel unwell.

5. Please keep it out of reach of children, Beware of Children's Mis-eating, and children under the age of 3 should not use it.

STOP USE

1. This product is for external use only and is not edible;

2. Avoid eye contact, if accidentally into the eyes, please rinse with water immediately;

3. Do not use it if you have dermatitis or skin damage;

4. Depending on the individual's physical condition, before use,It is recommended to have an allergy test behind the ear and stop using it immediately if you feel unwell.

5. Please keep it out of reach of children, Beware of Children's Mis-eating, and children under the age of 3 should not use it.

DO NOT USE

Depending on the individual's physical condition, before use,It is recommended to have an allergy test behind the ear and stop using it immediately if you feel unwell.

KEEP OUT OF REACH OF CHILDREN

Please keep it out of reach of children, Beware of Children's Mis-eating, and children under the age of 3 should not use it.

WHEN USING

Precautions:

1. This product is for external use only and is not edible;

2. Avoid eye contact, if accidentally into the eyes, please rinse with water immediately;

3. Do not use it if you have dermatitis or skin damage;

4. Depending on the individual's physical condition, before use,It is recommended to have an allergy test behind the ear and stop using it immediately if you feel unwell.

5. Please keep it out of reach of children, Beware of Children's Mis-eating, and children under the age of 3 should not use it.

INACTIVE INGREDIENT

WATER 58.60%
GLYCERIN 5%
BUTYLENE GLYCOL 1%
HYDROXYACETOPHENONE 2.00%
1,2-HEXANEDIOL 0.80%
WATER 0.80%
BUTYLENE GLYCOL 2.00%
PORTULACA OLERACEA EXTRACT 1.00%
GLYCERIN 1.20%
CHRYSANTHELLUM INDICUM EXTRACT 2.00%
PELARGONIUM GRAVEOLENS FLOWER/LEAF/STEM EXTRACT 2.00%
MENTHA ARVENSIS LEAF EXTRACT 2.00%
ALOE BARBADENSIS EXTRACT 2.00%
SOPHORA ANGUSTIFOLIA ROOT EXTRACT 2.00%
HYDROXYACETOPHENONE 2.00%
1,2-HEXANEDIOL 2.00%
POLYACRYLIC ACID 0.20%
PEG-40 HYDROGENATED CASTOR OIL 0.20%
CARBOMER 0.15%
SODIUM HYDROXIDE 0.12%
CUCUMIS SATIVUS (CUCUMBER) EXTRACT 3%
BUTYLENE GLYCOL 1.00%
HYDROXYACETOPHENONE 1.00%
SACCHAROMYCES FERMENT LYSATE FILTRATE 1.00%
1,2-HEXANEDIOL 1.00%
HYDROXYACETOPHENONE 1.00%
PENTYLENE GLYCOL 1.00%
BIFIDA FERMENT FILTRATE 0.20%
1,2-HEXANEDIOL 0.80%
HYDROXYACETOPHENONE 0.10%
TREHALOSE 1.00%
BETAINE 1.00%
ALOE BARBADENSIS LEAF WATER 1.00%
ALLANTOIN 1.00%
CAPRYLHYDROXAMIC ACID 1.00%
FRAGRANCE 1.00%
FRAGRANCE 1.20%
SODIUM CHLORIDE 1.00%
CI 19140 1.00%
CI 42090 1.00%
WATER 1.20%
BUTYLENE GLYCOL 1.20%
BACILLUS/SOYBEAN FERMENT EXTRACT 0.20%
FOLIC ACID 0.20%
1,2-HEXANEDIOL 0.20%
SODIUM HYALURONATE 0.20%
WATER 0.20%
GLYCERIN 1.20%
1,2-HEXANEDIOL 1.20%
SOLUBLE COLLAGEN 1.20%
MALTODEXTRIN 1.20%
CENTELLA ASIATICA EXTRACT 1.20%
BISABOLOL 1.20%
FARNESOL 1.20%
DIPOTASSIUM GLYCYRRHIZATE 1.20%